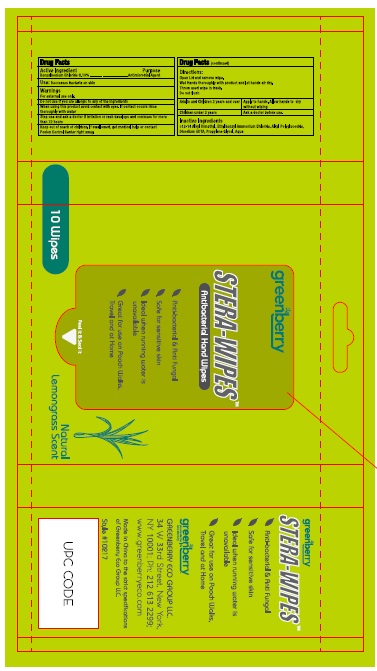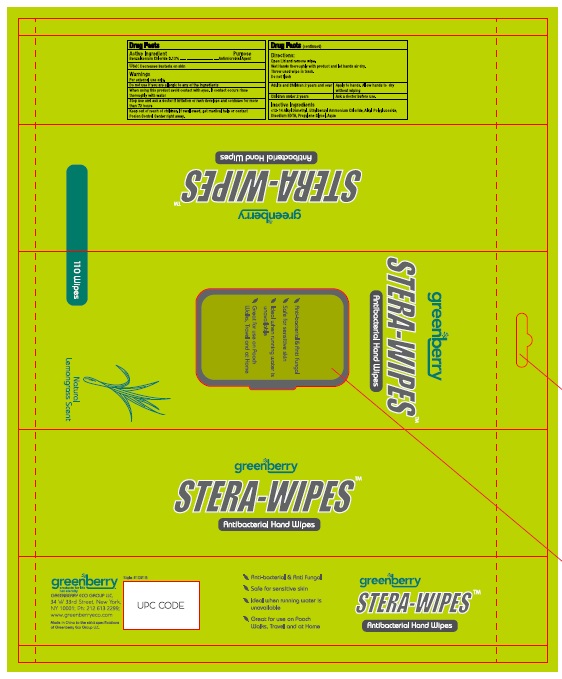 DRUG LABEL: Greenberry
NDC: 77965-001 | Form: CLOTH
Manufacturer: Greenberry Eco Group LLC
Category: otc | Type: HUMAN OTC DRUG LABEL
Date: 20200609

ACTIVE INGREDIENTS: Benzalkonium Chloride 1.3 g/100 mL
INACTIVE INGREDIENTS: N-ALKYL ETHYLBENZYL DIMETHYL AMMONIUM (C12-C14); DECYL GLUCOSIDE; EDETATE DISODIUM ANHYDROUS; PROPYLENE GLYCOL; WATER

Active Ingredient

Benzalkonium Chloride 0.13%

Purpose

Antimicrobial agent

Uses

Decreases bacteria on skin.

Warnings

For external use only.

Do not use if you are allergic to any of the ingredients.

When using this product avoid contact with eyes. If contact occurs, rinse thoroughly with water.

Stop use and ask a doctor if irritation or rash develops and continues for more than 72 hours.

Keep out of reach of children. If swallowed, get medical help or contact a Poison Control Center right away.

Directions

Open lid and remove wipes.
Wet hands thoroughly with product and let hands air dry.
Throw used wipe in trash.
Do not flush.

Adults and children 2 years and over: | Apply to hands. allow hands to dry without wiping.
Children under 2 years: | Ask a doctor before use.

Inactive ingredients

c12-14 Alkyl Dymethyl, Ethylbenzyl Ammonium Chloride, Alkyl Polyglucoside, Disodium EDTA, Propylene glycol, Aqua

Package Label - Principal Display Panel

Label, 10 Wipes

Label 110 Wipes